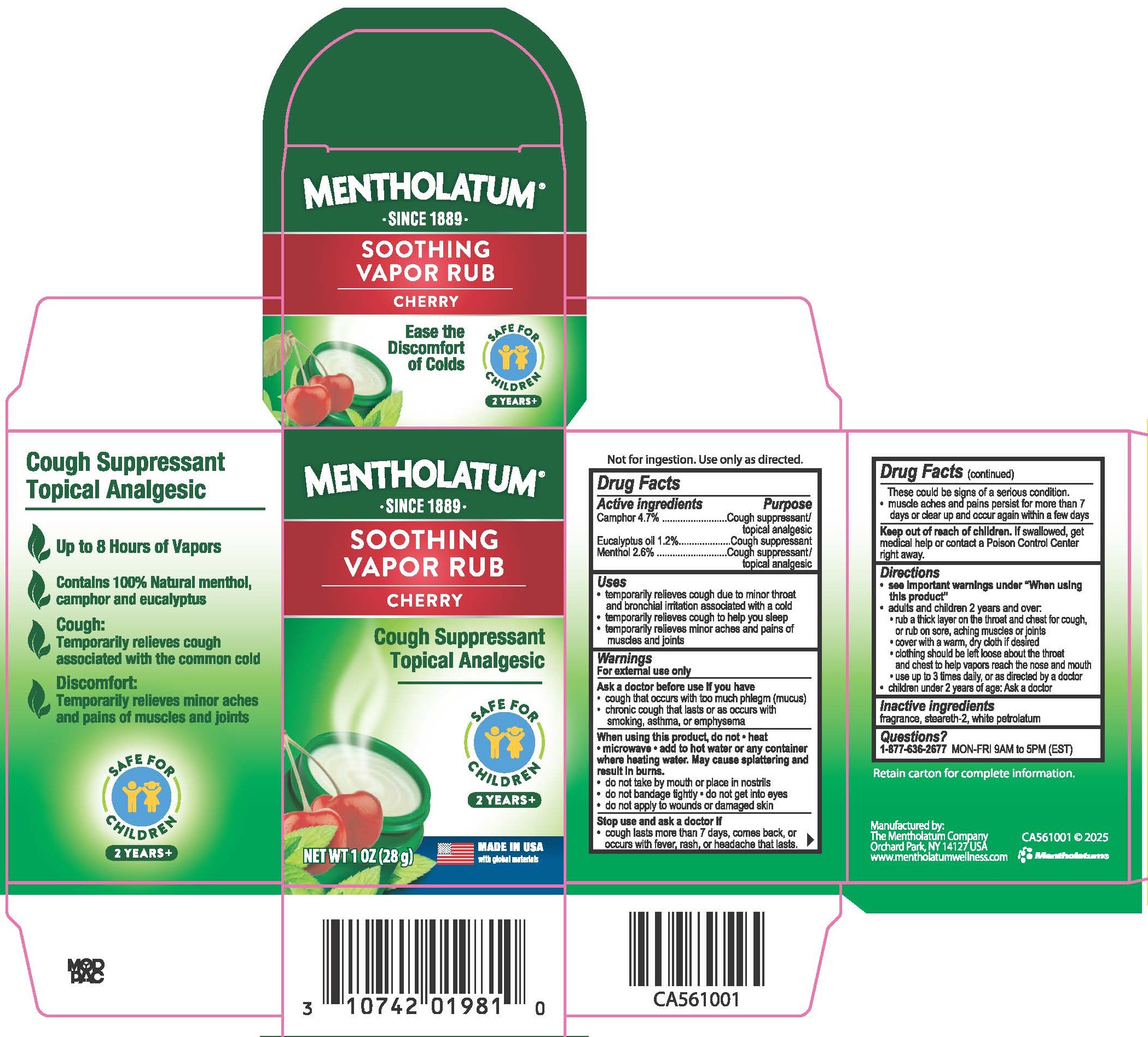 DRUG LABEL: Mentholatum Soothing Vapor Rub Cherry
NDC: 10742-1062 | Form: OINTMENT
Manufacturer: The Mentholatum Company
Category: otc | Type: HUMAN OTC DRUG LABEL
Date: 20260114

ACTIVE INGREDIENTS: MENTHOL 28 mg/1 g; CAMPHOR, (-)- 28 mg/1 g; EUCALYPTUS OIL 28 mg/1 g
INACTIVE INGREDIENTS: STEARETH-2; FRAGRANCE 13576; WHITE PETROLATUM

Drug Facts - Mentholatum Soothing Vapor Rub Cherry

Active ingredients

Camphor 4.7%

Eucalyptus oil 1.2%

Menthol 2.6%

Purpose

Camphor - Cough suppressant / topical analgesic

Eucalyptus oil - Cough suppressant

Menthol - Cough suppressant / topical analgesic

Uses

- temporarily relieves cough due to minor throat and bronchial irritation associated with a cold
- temporarily relieves cough to help you sleep
- temporarily relieves minor aches and pains of muscles and joints

Warnings

For external use only

Ask a doctor before use if you have

- cough that occurs with too much phlegm (mucus)
- chronic cough that lasts or as occurs with smoking, asthma, or emphysema

When using this product,

do not,

- heat
- microwave
- add to hot water or any container where heating water. May cause splattering and result in burns.
- do not take by mouth or place in nostrils
- do not bandage tightly
- do not get into eyes
- do not apply to wounds or damaged skin

Stop use and ask a doctor if

- cough lasts more than 7 days, comes back, or occurs with fever, rash, or headache that lasts. These could be signs of a serious condition.
- muscle aches and pains worsen, persist for more than 7 days, or clear up and occur again within a few days

Keep out of reach of children.

If swallowed, get medical help or contact a Poison Control Center right away.

Directions

- see important warnings under "When using this product"
- adults and children 2 years and over:
- rub a thick layer on the throat and chest for cough, or rub on sore, aching muscles or joints
- cover with a warm, dry cloth if desired
- clothing should be left loose about the throat and chest to help vapors reach the nose and mouth
- use up to 3 times daily, or as directed by a doctor
- children under 2 years of age: Ask a doctor

Inactive ingredients

fragrance, steareth-2, white petrolatum

Questions?

1-877-636-2677 MON-FRI 9AM to 5 PM (EST)